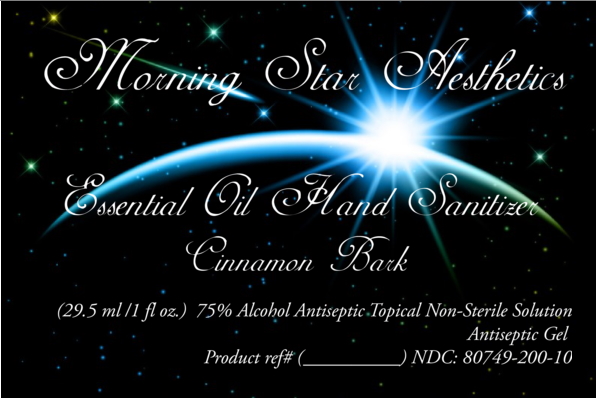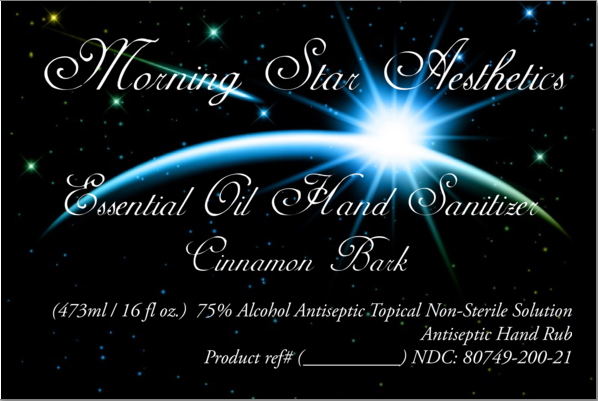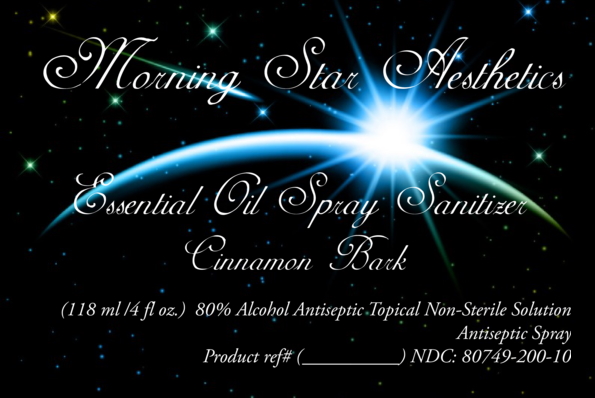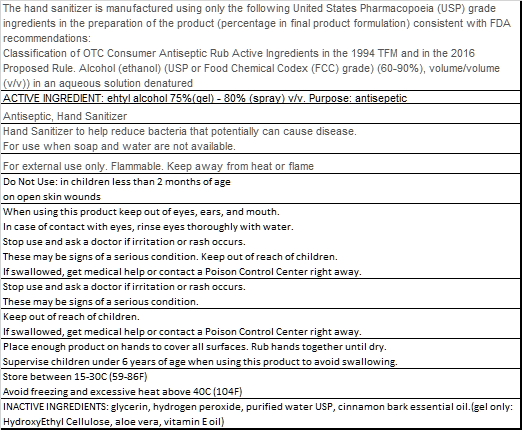 DRUG LABEL: cinnamon bark sanitizer
NDC: 80749-100 | Form: SPRAY
Manufacturer: Morning Star Aesthetics
Category: otc | Type: HUMAN OTC DRUG LABEL
Date: 20201002

ACTIVE INGREDIENTS: ALCOHOL 23.66 mL/29.57 mL
INACTIVE INGREDIENTS: CINNAMON OIL 0.09 mL/29.57 mL; WATER 5.36 mL/29.57 mL; GLYCERIN 0.43 mL/29.57 mL; HYDROGEN PEROXIDE 0.04 mL/29.57 mL

The hand sanitizer is manufactured using only the following United States Pharmacopoeia (USP) grade ingredients in the preparation of the product (percentage in final product formulation) consistent with FDA recommendations: Classification of OTC Consumer Antiseptic Rub Active Ingredients in the 1994 TFM and in the 2016 Proposed Rule. Alcohol (ethanol) (USP or Food Chemical Codex (FCC) grade) (60-90%), volume/volume (v/v)) in an aqueous solution denatured

Active Ingredient(s)

Alcohol 75%(Gel) - 80% (Spray) v/v. Purpose: Antiseptic

Purpose

Antiseptic, Hand Sanitizer

Use

Hand Sanitizer to help reduce bacteria that potentially can cause disease. For use when soap and water are not available.

Warnings

For external use only. Flammable. Keep away from heat or flame

Do not use

- in children less than 2 months of age
- on open skin wounds

When using this product keep out of eyes, ears, and mouth. In case of contact with eyes, rinse eyes thoroughly with water.
Stop use and ask a doctor if irritation or rash occurs. These may be signs of a serious condition.
Keep out of reach of children. If swallowed, get medical help or contact a Poison Control Center right away.

Stop use and ask a doctor if irritation or rash occurs. These may be signs of a serious condition.

Keep out of reach of children. If swallowed, get medical help or contact a Poison Control Center right away.

Directions

- Place enough product on hands to cover all surfaces. Rub hands together until dry.
- Supervise children under 6 years of age when using this product to avoid swallowing.

Other information

- Store between 15-30C (59-86F)
- Avoid freezing and excessive heat above 40C (104F)

Inactive ingredients

glycerin, hydrogen peroxide, purified water USP, Cinnamon Bark Essential Oil

Package Labels - Front and Rear

Essential Oil Sanitizer Spray Cinnamon Bark 4oz

(118 ml /4 fl oz) NDC: 80749-200-10

Essential Oil Hand Sanitizer Cinnamon Bark 1oz

(29.5 ml /1 fl oz.) NDC: 80749-200-20

Essential Oil Hand Sanitizer Cinnamon Bark 16oz

(473ml / 16 fl oz.) NDC: 80749-200-21

Sanitizer Rear Label